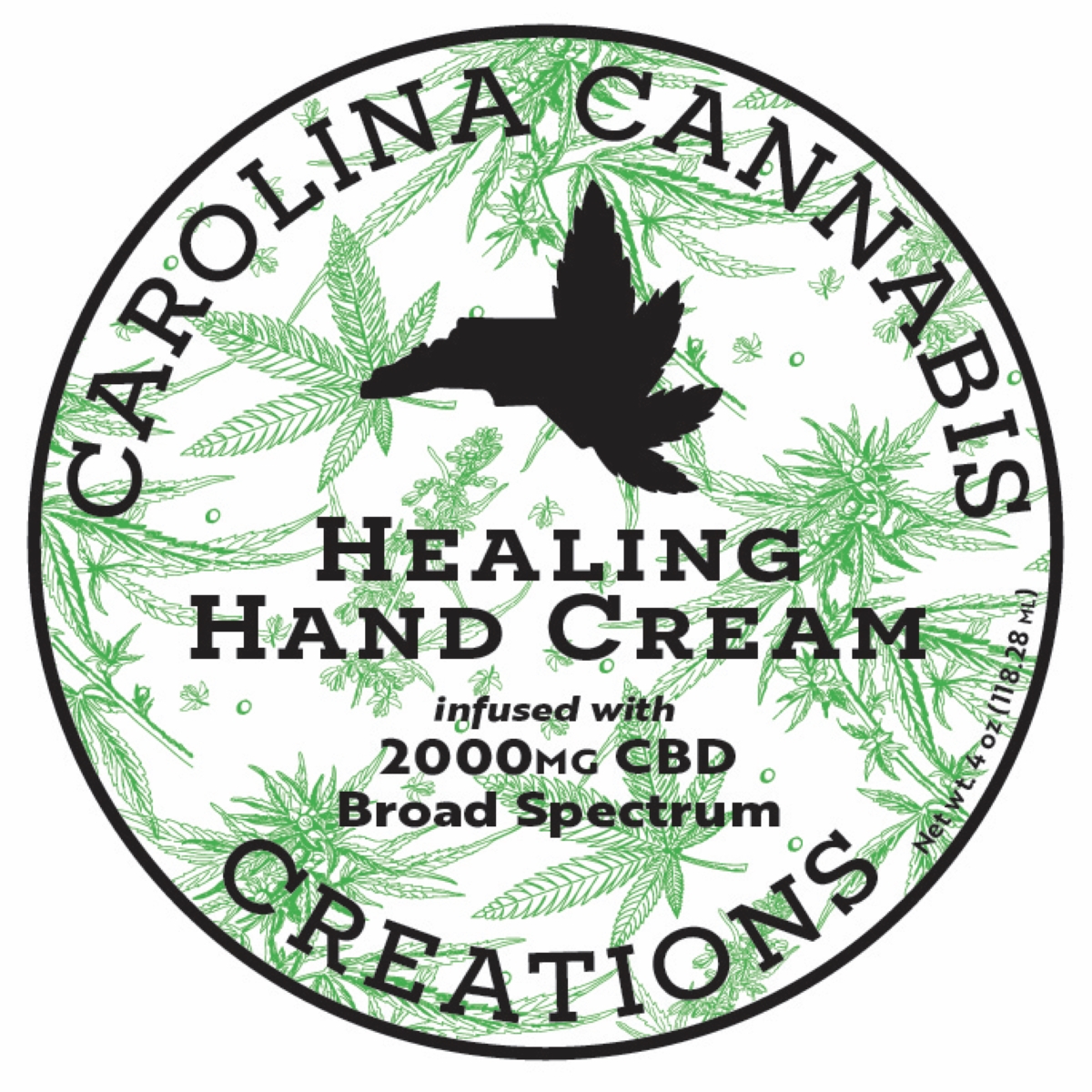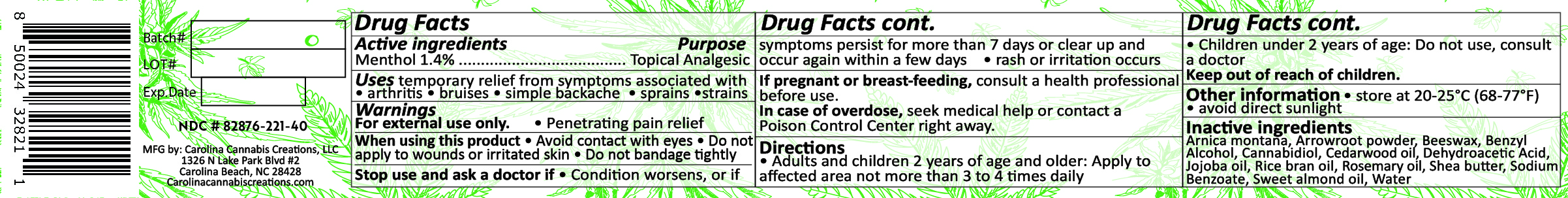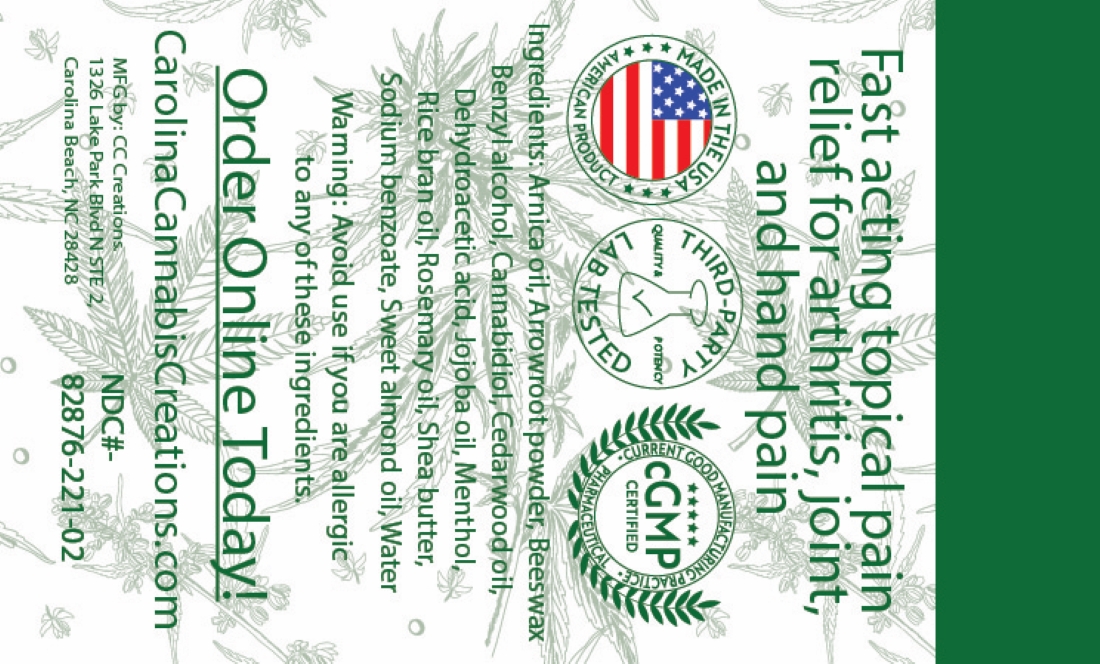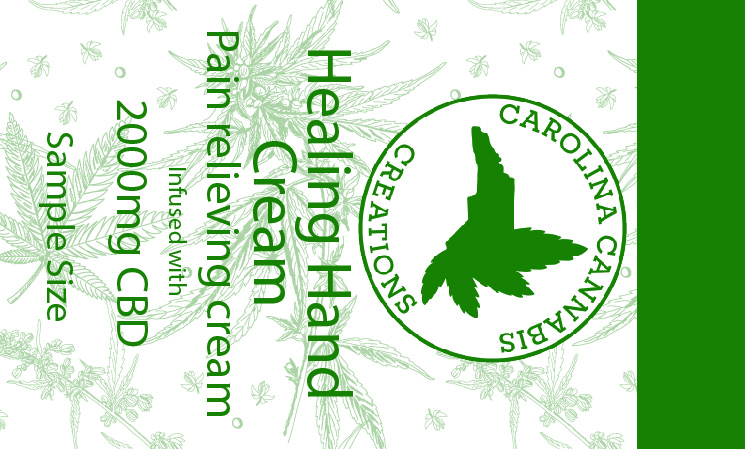 DRUG LABEL: Healing Hand Cream 2000mg
NDC: 82876-221 | Form: SALVE
Manufacturer: Carolina Cannabis Creations LLC
Category: otc | Type: HUMAN OTC DRUG LABEL
Date: 20250115

ACTIVE INGREDIENTS: MENTHOL 1.4 g/111.45 g
INACTIVE INGREDIENTS: XANTHAN GUM 0.35 g/111.45 g; SODIUM BENZOATE 0.15 g/111.45 g; DEHYDROACETIC ACID 0.1 g/111.45 g; BENZYL ALCOHOL 0.97 g/111.45 g; JOJOBA OIL 3.82 g/111.45 g; PEG-8 BEESWAX 19.9 g/111.45 g; ALMOND OIL 17.48 g/111.45 g; ROSEMARY OIL 0.59 g/111.45 g; RICE BRAN OIL 19.04 g/111.45 g; SHEA BUTTER 15.07 g/111.45 g; CANNABIDIOL 2.25 g/111.45 g; ARNICA MONTANA FLOWER WATER 4.21 g/111.45 g; MARANTA ARUNDINACEA ROOT 0.86 g/111.45 g; WATER 24.64 g/111.45 g; CEDRUS ATLANTICA WOOD OIL 0.62 g/111.45 g

Active Ingredients

Menthol...........1.4%

Purpose

Menthol 1.4%.........................Topical Analgesic

Uses

Temporary relief of aches and pains associated with arthritis, backache, joint pain, muscle strains, and sprains

Warnings

FOR EXTERNAL USE ONLY, provides penetrating pain relief

When using this product

Do not apply to wounds or irritated skin, and avoid contact with eyes

Stop use and ask a doctor if

The condition worsens, symptoms last more than 7 days, the condition clears but occurs again within a few days, Rash or irritation occurs

Stop use and ask a doctor if

Condition worsens, Symptoms last more than 7 days, Condition clears up but occurs again within a few days, Rash or irritations occurs

If pregnant or breastfeeding

Consult a health professional before use

In case of an overdose

seek medical help or contact a poison control center right away

Directions

Adults and children 12 years and over; apply to the affected area one to four times daily

Children 12 years and younger; ask a doctor

Keep out of reach of children

Keep out of reach of children

Other information

Store at 68-77 degrees F, Avoid direct sunlight

Inactive ingredients

Arnica Montana oil, Arrowroot powder, Beeswax, Benzyl alcohol, Cannabidiol, Cedarwood oil, Dehydroacetic acid, Jojoba oil, Rice bran oil, Rosemary oil, Shea butter, Sodium Benzoate, Sweet almond oil, water, Xanthan Gum.